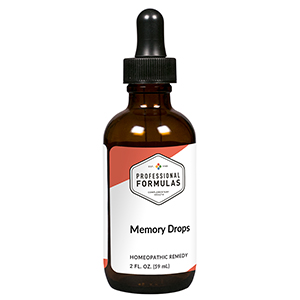 DRUG LABEL: Memory Drops
NDC: 63083-2043 | Form: LIQUID
Manufacturer: Professional Complementary Health Formulas
Category: homeopathic | Type: HUMAN OTC DRUG LABEL
Date: 20190815

ACTIVE INGREDIENTS: AVENA SATIVA FLOWERING TOP 2 [hp_X]/59 mL; CHOLINE 2 [hp_X]/59 mL; BOS TAURUS BRAIN 6 [hp_X]/59 mL; LYCOPODIUM CLAVATUM SPORE 3 [hp_X]/59 mL; ZINC 3 [hp_X]/59 mL; GLUTAMIC ACID 6 [hp_X]/59 mL; DELPHINIUM STAPHISAGRIA SEED 6 [hp_X]/59 mL; BARIUM CARBONATE 6 [hp_X]/59 mL; ANHYDROUS DIBASIC CALCIUM PHOSPHATE 6 [hp_X]/59 mL; POTASSIUM PHOSPHATE, UNSPECIFIED FORM 6 [hp_X]/59 mL; SEMECARPUS ANACARDIUM JUICE 6 [hp_X]/59 mL; LEAD 12 [hp_X]/59 mL
INACTIVE INGREDIENTS: ALCOHOL; WATER

C43

ACTIVE INGREDIENTS

Avena sativa 2X, 3X
Choline 2X, 3X
Brain 6X
Lycopodium clavatum 3X, 6X
Zincum metallicum 3X, 6X
Glutamic acid 6X
Staphysagria 6X
Baryta carbonica 6X, 12X
Calcarea phosphorica 6X, 12X
Kali phosphoricum 6X, 12X
Anacardium orientale 6X, 12X, 30X
Plumbum metallicum 12X

QUESTIONS

Professional Formulas

PO Box 2034 Lake Oswego, OR 97035

INDICATIONS

For the temporary relief of weakened memory, absentmindedness, difficulty focusing, or confusion.*

PURPOSE

*Claims based on traditional homeopathic practice, not accepted medical evidence. Not FDA evaluated.

WARNINGS

In case of overdose, get medical help or contact a poison control center right away.

Keep out of the reach of children.

PREGNANCY OR BREAST FEEDING

If pregnant or breastfeeding, ask a healthcare professional before use.

DIRECTIONS

Place drops under tongue 30 minutes before/after meals. Adults and children 12 years and over: Take 10 drops up to 3 times per day. Consult a physician for use in children under 12 years of age.

OTHER INFORMATION

Tamper resistant. If seal is broken, do not use. After opening, close container tightly and store at room temperature away from heat.

INACTIVE INGREDIENTS

20% ethanol, purified water.

LABEL

Est 1985

Professional Formulas

Complementary Health

Memory Drops

Homeopathic Remedy

2 FL. OZ. (59 mL)